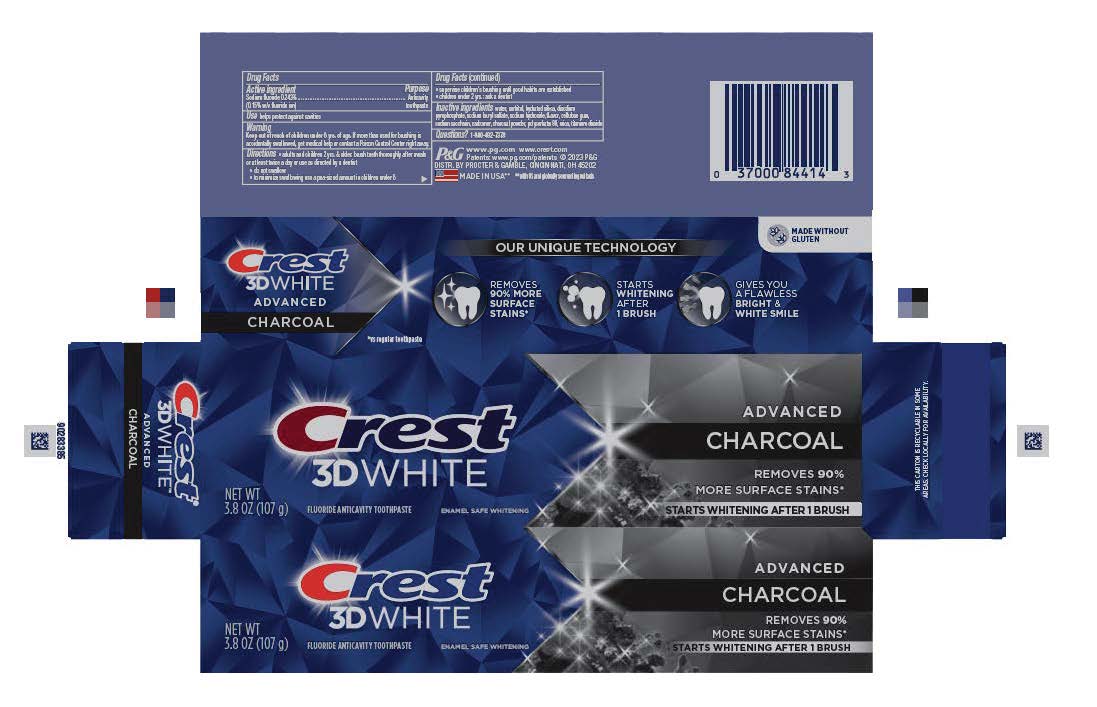 DRUG LABEL: Crest 3D White
NDC: 69423-767 | Form: PASTE, DENTIFRICE
Manufacturer: The Procter & Gamble Manufacturing Company
Category: otc | Type: HUMAN OTC DRUG LABEL
Date: 20260108

ACTIVE INGREDIENTS: SODIUM FLUORIDE 1.5 mg/1 g
INACTIVE INGREDIENTS: SODIUM HYDROXIDE; POLYSORBATE 80; SODIUM ACID PYROPHOSPHATE; SORBITOL; CARBOXYMETHYLCELLULOSE SODIUM; HYDRATED SILICA; WATER; SODIUM LAURYL SULFATE; SACCHARIN SODIUM; MICA; TITANIUM DIOXIDE; CARBOXYPOLYMETHYLENE; ACTIVATED CHARCOAL

Crest 3D White Advanced Charcoal

Drug Facts

Active ingredient

Sodium fluoride 0.243% (0.15% w/v fluoride ion)

Purpose

Anticavity toothpaste

Use

helps protect against cavities

Warning

Keep out of reach of children under 6 yrs. of age. If more than used for brushing is accidentally swallowed, get medical help or contact a Poison Control Center right away.

Directions

- adults and children 2 yrs. & older: brush teeth thoroughly after meals or at least twice a day or use as directed by a dentist
- do not swallow
- to minimize swallowing use a pea-sized amount in children under 6
- supervise children's brushing until good habits are established
- children under 2 yrs.: ask a dentist

Inactive ingredients

water, sorbitol, hydrated silica, disodium
pyrophosphate, sodium lauryl sulfate, sodium hydroxide, flavor, cellulose gum,
sodium saccharin, carbomer, charcoal powder, polysorbate 80, mica, titanium
dioxide

Questions?

1-800-492-7378

DISTR. BY PROCTER & GAMBLE, CINCINNATI, OH 45202

PRINCIPAL DISPLAY PANEL - 107 g Tube Carton

Crest

3D WHITE

NET WT

3.8 OZ (107 g)

FLUORIDE ANTICAVITY TOOTHPASTE

ENAMEL SAFE WHIENENING

ADVANCED

CHARCOAL

REMOVES 90%

MORE SUFACE STAINS*

STARTS WHITENING AFTER 1 BRUSH